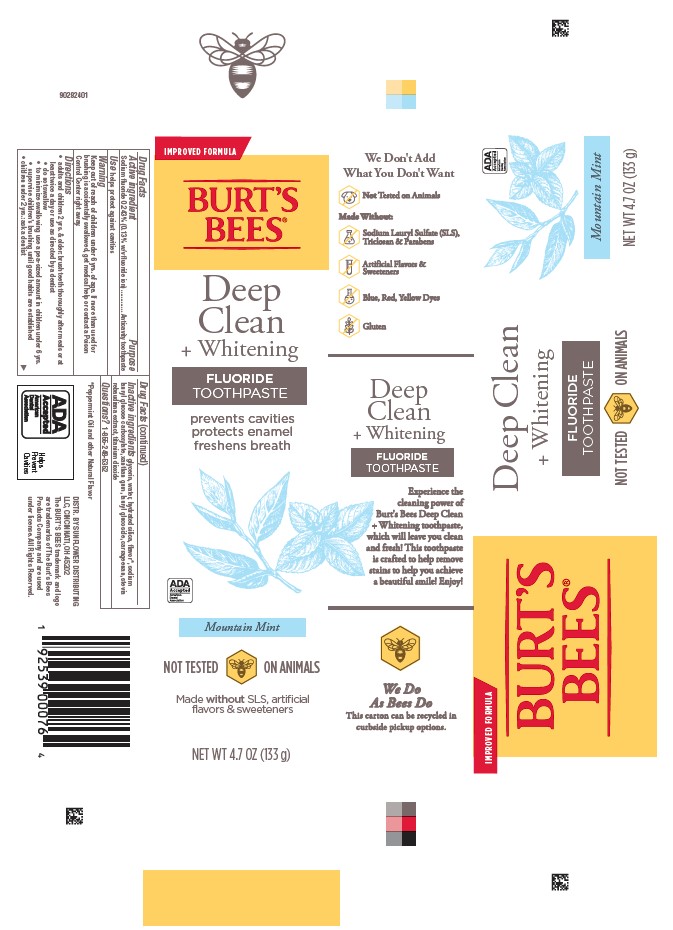 DRUG LABEL: Burts Bees
NDC: 69423-961 | Form: PASTE, DENTIFRICE
Manufacturer: Procter & Gamble Manufacturing Company
Category: otc | Type: HUMAN OTC DRUG LABEL
Date: 20250410

ACTIVE INGREDIENTS: SODIUM FLUORIDE 1.3 mg/1 g
INACTIVE INGREDIENTS: CARRAGEENAN; TITANIUM DIOXIDE; XANTHAN GUM; WATER; HYDRATED SILICA; GLYCERIN; STEVIA REBAUDIANA WHOLE; SODIUM LAURYL GLYCOL CARBOXYLATE; LAURYL GLUCOSIDE

Burt's Bees Deep Clean + Whitening

Drug Facts

Active ingredient

Sodium fluoride 0.243% (0.13% w/v fluoride ion)

Purpose

Anticavity toothpaste

Use

helps protect against cavities

Warnings

Keep out of reach of children under 6 yrs of age. If more than used for brushing is accidentally swallowed, get medical help or contact a Poison Control Center right away.

Directions

- adults and children 2 yrs. & older: brush teeth thoroughly after meals or at least twice a day or use as directed by a dentist
- do not swallow
- to minimize swallowing use a pea-sized amount in children under 6
- supervise children’s brushing until good habits are established
- children under 2 yrs.: ask a dentist

Inactive ingredients

glycerin, water, hydrated silica, flavor*, sodium
lauryl glucose carboxylate, xanthan gum, lauryl glucoside, carrageenan, stevia
rebaudiana extract, titanium dioxide

Questions?

1-855-248-5352

*Peppermint Oil and other Natural Flavor

DISTR. BY SUNFLOWER DISTRIBUTING
LLC, CINCINNATI, OH 45202

PRINCIPAL DISPLAY PANEL - 133 g tube in carton

Improved Formula

BURT'S

BEES®

Deep

Clean

+ Whitening

FLUORIDE

Toothpaste

prevents cavities
protects enamel
freshens breath

ADA

Accepted

American

Dental

Association

Mountain Mint

NOT TESTED ON ANIMALS

Madewithout SLS,
artificial flavors & sweeteners

NET WT 4.7 OZ (133 g)